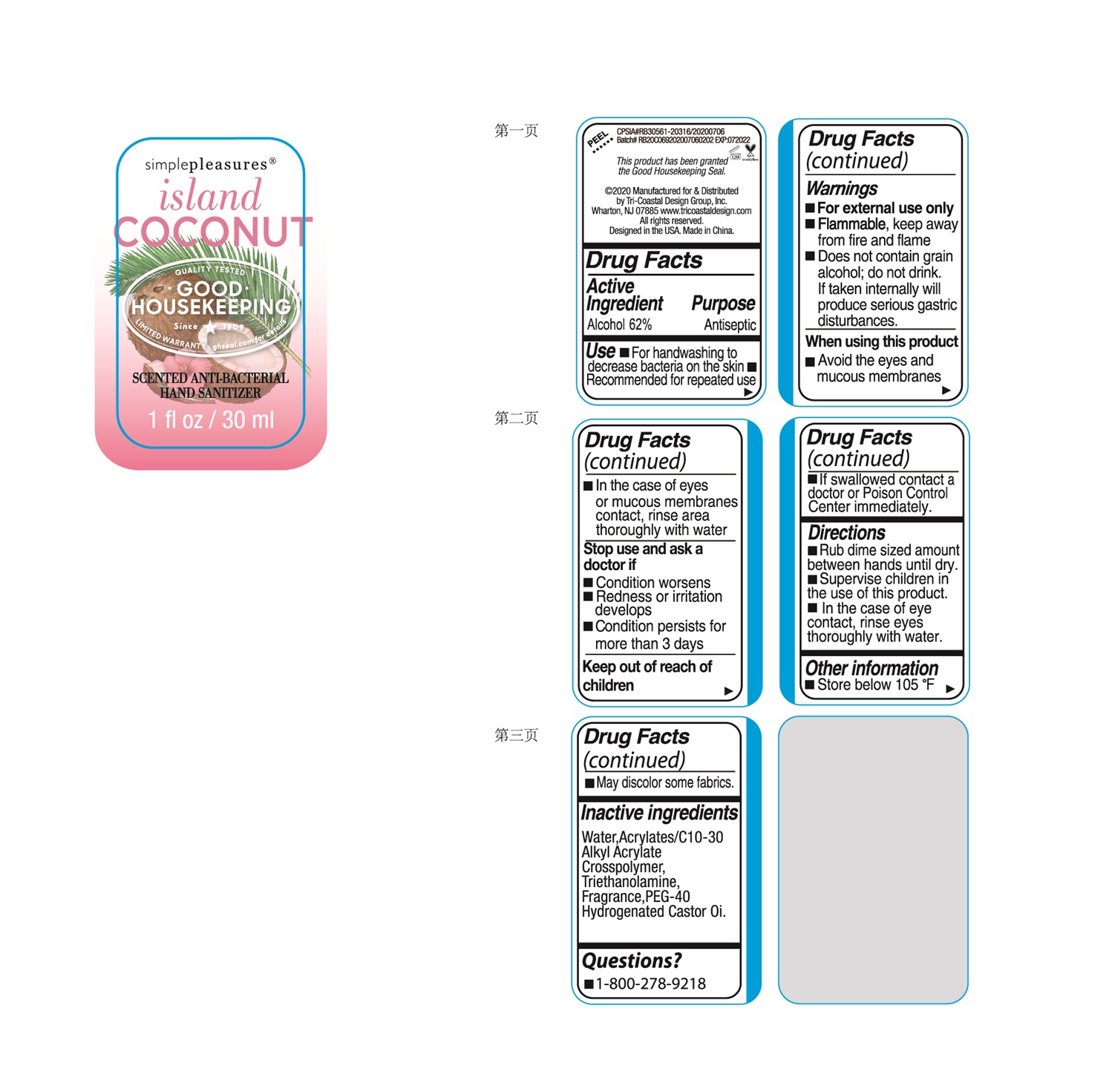 DRUG LABEL: HAND SANITIZER
NDC: 73549-010 | Form: GEL
Manufacturer: Fortress Expert Co., Ltd
Category: otc | Type: HUMAN OTC DRUG LABEL
Date: 20200803

ACTIVE INGREDIENTS: ALCOHOL 62 mL/100 mL
INACTIVE INGREDIENTS: POLYOXYL 40 HYDROGENATED CASTOR OIL; WATER; TROLAMINE; CARBOMER INTERPOLYMER TYPE A (ALLYL SUCROSE CROSSLINKED)

FrtressTricstlClearlHndSntzrAlch62

Active ingredient

Alcohol 62%

Purpose

Antiseptic

Use

■ For handwashing to decrease bacteria on the skin ■ Recommended for repeated use

Warnings

■ For external use only

■ Flammable, keep away from open flame and sources of heat

■ Does not contain grain alcohol; do not drink. If taken internally will produce gastric distrubances.

When using this product

■ Avoid the eyes and mucoous membranes

■ In the case of eyes or mucous membranes contacr, rinse area thoroughly with water

Stop use and ask a doctor if

■ Condition worsens

■ Redness or irritation develops

■ Condition persists for more than 3 days

Keep out of reach of children

■ If swallowed, contact a doctor or Poison Control Center immediately

Directions

■ Rub dime sized amount between hands until dry.

■ Supervise children in the use of this product.

■ In the case of eye contact, rinse eyes thoroughly with water.

Other information

■ Store below 105ºF

■ May discolor some fabrics.

Inactive ingredients

Water, Acrylates/C10-30 Alkyl Acrylate Crosspolymer, Triethanolamine, Fragrance, PEG-40 Hydrogenated Castor Oil

Questions?

■ 1-800-278-9218